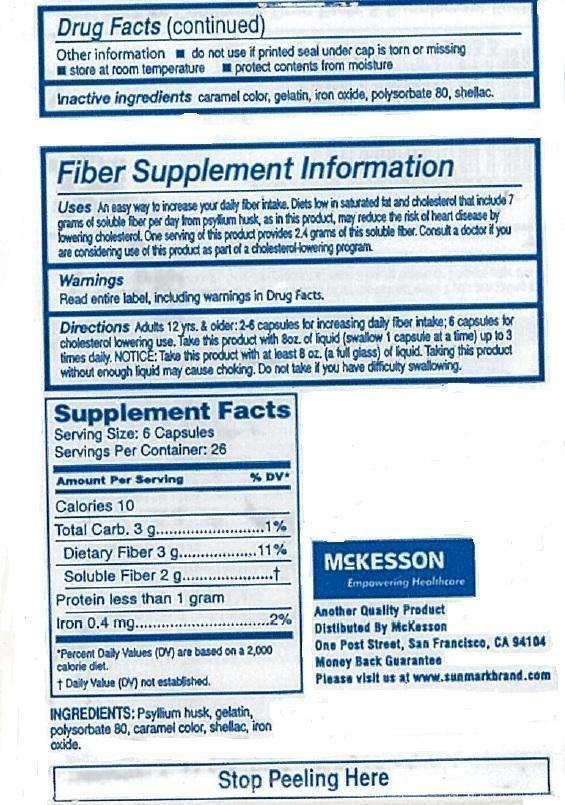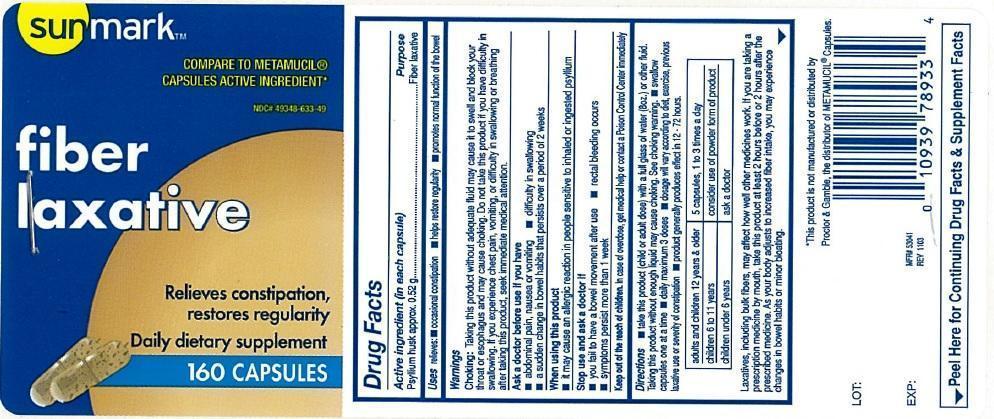 DRUG LABEL: Fiber laxative
NDC: 49348-633 | Form: CAPSULE
Manufacturer: McKesson
Category: otc | Type: HUMAN OTC DRUG LABEL
Date: 20140410

ACTIVE INGREDIENTS: PSYLLIUM HUSK 520 mg/1 1
INACTIVE INGREDIENTS: CARAMEL; GELATIN; BROWN IRON OXIDE; POLYSORBATE 80; SHELLAC

Sunmark Fiber Laxative

Active ingredient (in each capsule)

Psyllium husk approx. 0.52 g

Purpose

Fiber laxative

Uses

relieves:

- occasional constipation
- helps restore regularity
- promotes normal function of the bowel

Warnings

Choking: Taking this product without adequate fluid may cause it to swell and block your throat or esophagus and may cause choking. Do not take this product if you have difficulty in swallowing. If you experience chest pain, vomiting, or difficulty in swallowing or breathing after taking this product, seek immediate medical attention.

Ask a doctor before use if you have

- abdominal pain, nausea or vomiting
- difficulty in swallowing
- a sudden change in bowel habits that persists over a period of 2 weeks

When using this product

- it may cause an allergic reaction in people sensitive to inhaled or ingested psyllium

Stop use and ask a doctor if

- you fail to have a bowel movement after use
- rectal bleeding occurs
- symptoms persist more than 1 week
- Keep out of reach of children. In case of overdose, get medical help or contact a Poison Control Center immediately

Directions

- take this product (child or adult dose) with a full glass of water (8oz.) or other fluid. Taking this product without enough liquid may cause choking. See choking warning.
- swallow capsules one at a time
- daily maximum 3 doses
- dosage will vary according to diet, exercise, previous laxative use or severity of constipation.
- product generally produces effect in 12-72 hours.

adults and children 12 years and older | 5 capsules, 1 to 3 times a day
children 6 to under 11 years | consider use of powder form of product
children under 6 years | ask a doctor

- Laxatives, including bulk fibers, may affect how well other medicines work. If you are taking a prescription medicine by mouth, take this product at least 2 hours before or 2 hours after the prescribed medicine. As your body adjusts to increased fiber intake, you may experience changes in bowel habits or minor bloating.

Other information

- do not use if printed seal under cap is torn or missing.
- store at room temperature
- protect contents from moisture.

Inactive ingredients

caramel color, gelatin, iron oxide, polysorbate 80, shellac

Fiber Supplement information

Uses: An easy way to increase your daily fiber intake. Diets low in saturated fat and cholesterol that include 7 grams of soluble fiber per day from psyllium husk, as in this product, may reduce the risk of heart disease by lowering cholesterol. One serving of this product provides 2.4 grams of this soluble fiber. consult a doctor if you are considering use of this product as part of a cholesterol lowering program.

Warnings: Read entire label, including warnings in Drug Facts

Directions: Adults 12 years and older: 2-6 capsules for increasing daily fiber intake; 6 capsules for cholesterol lowering use. Take this product 8oz. of liquid (swallow 1 capsule at a time) up to 3 times daily. NOTICE: Take this product atleast 8 oz . (a full glass) of liquid. Taking this product without enough liquid may cause choking. Do not take if you have difficulty swallowing.

PDP

Sunmark

compare to Metamucil® capsules active ingredient

fiber laxative

Relieves constipation, restores regularity

dietary fiber supplement

160 capsules